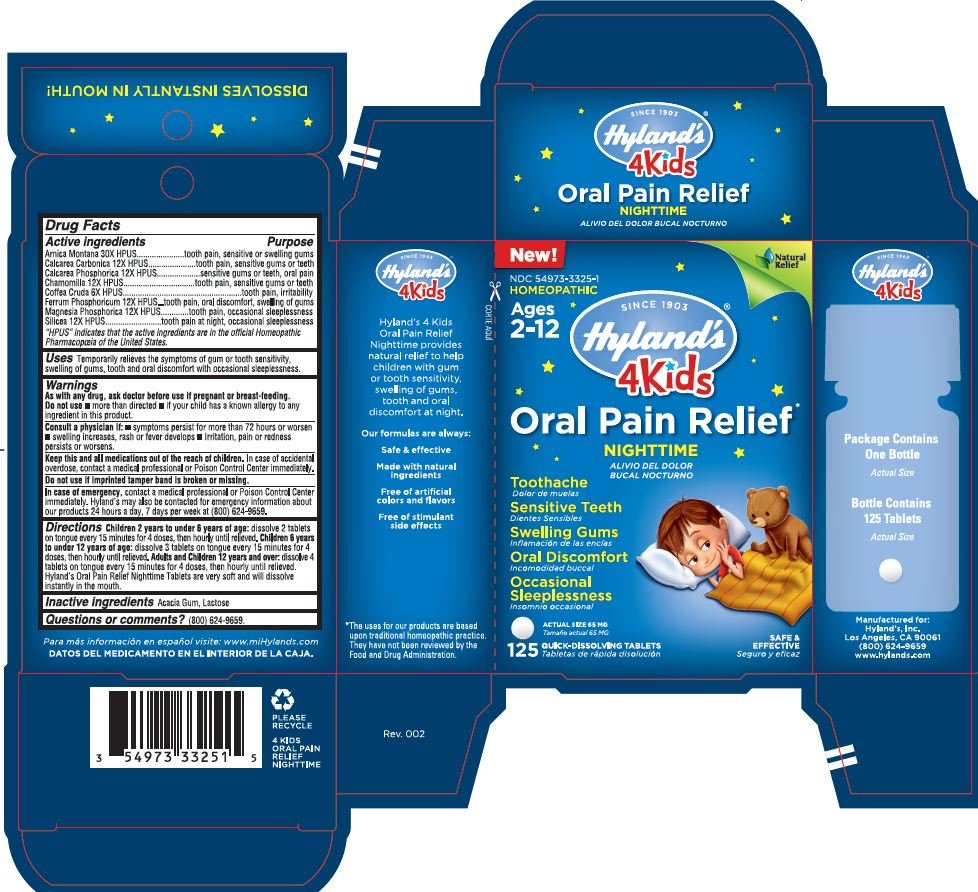 DRUG LABEL: 4 Kids Oral Pain Relief Nighttime
NDC: 54973-3325 | Form: TABLET
Manufacturer: Hyland's Inc.
Category: homeopathic | Type: HUMAN OTC DRUG LABEL
Date: 20221122

ACTIVE INGREDIENTS: OYSTER SHELL CALCIUM CARBONATE, CRUDE 12 [hp_X]/1 g; MAGNESIUM PHOSPHATE, DIBASIC TRIHYDRATE 12 [hp_X]/1 g; ARABICA COFFEE BEAN 6 [hp_X]/1 g; FERRUM PHOSPHORICUM 12 [hp_X]/1 g; SILICON DIOXIDE 12 [hp_X]/1 g; ARNICA MONTANA 30 [hp_X]/1 g; TRIBASIC CALCIUM PHOSPHATE 12 [hp_X]/1 g; MATRICARIA CHAMOMILLA 12 [hp_X]/1 g
INACTIVE INGREDIENTS: ACACIA; LACTOSE MONOHYDRATE

4 Kids Oral Pain Relief Nighttime

Drug Facts

Active Ingredients | Purpose
Arnica Montana 30X HPUS | tooth pain, sensitive or swelling gums
Calcarea Carbonica 12X HPUS | tooth pain, sensitive gums or teeth
Calcarea Phosphorica 12X HPUS | sensitive gums or teeth, oral pain
Chamomilla 12X HPUS | tooth pain, sensitive gums or teeth
Coffea Cruda 6X HPUS | tooth pain, irritability, oral pain
Ferrum Phosphoricum 12X HPUS | tooth pain, oral discomfort, swelling of gums
Magnesia Phosphoricum 12X HPUS | tooth pain, occasional sleeplessness
Silicea 12X HPUS | tooth pain at night, occcasional sleeplessness

"HPUS" indicates that the active ingredients are in the official Homeopathic Pharmacopœia of the United States.

Uses

Temporarily relieves the symptoms of gum or tooth sensitivity, swelling of gums, tooth and oral disconfort with occasional sleeplessness.

WARNINGS

As with any drug, ask doctor before use if pregnant or breast-feeding.

Do not use • more than directed • if your child has known allergy to any ingredient in this product.

Consult a physician if:

• symptoms persist for more than 72 hours or worsen

• swelling increases, rash or fever develops

• Irritation, pain or redness persist or worsens

KEEP OUT OF REACH OF CHILDREN

Keep this and all medication out of the reach of children. In case of accidental overdose, contact a medical professional or Poison Control Center immediately.

Do not use if imprinted tamper band is broken or missing.

In case of an emergency

contact a medical professional or Poison Control Center immediately. Hyland's may also be contacted for emeregency information about our products 24 hours a day, 7 days per week at (800)624-9659

Directions

Children 2 years to under 6 years of age: dissolve 2 tablets on tongue every 15 minutes for 4 doses, then hourly until relieved.

Children 6 years to under 12 years of age: dissolve 3 tablets on tongue every 15 minutes for 4 doses, then hourly until relieved.

Adults and Children 12 years and over: dissolve 4 tablets on tongue every 15 minutes for 4 doses, then hourly until relieved.

Hyland's Oral Pain Relief Nighttime Tablets are very soft and will dissolve instantly in the mouth.

INACTIVE INGREDIENT

Acacia Gum, Lactose

Questions or comments?

(800) 624-9659.

PURPOSE

Oral pain relief

PRICIPAL DISPLAY PANEL - 125 TABLET CARTON

New!

NDC 54973-3325-1

HOMEOPATHIC

Natural

Relief

Ages

2-12

SINCE 1903

Hyland's

4Kids

Oral Pain Relief

NIGHTTIME

Toothache

Sensitive Teeth

Swelling Gums

Oral Disconfort

Occasional Sleeplessness

ACTUAL SIZE 65 MG

125 QUICK-DISSOLVING TABLETS

SAFE & EFFECTIVE